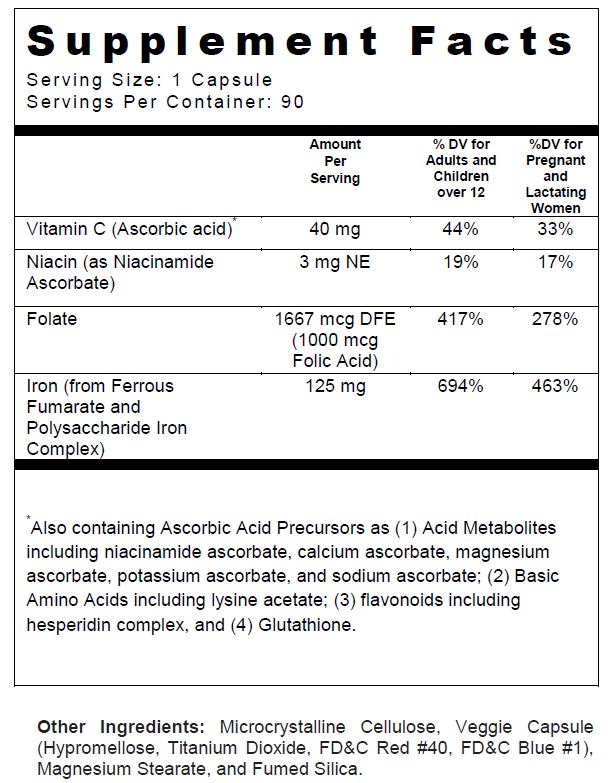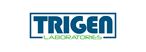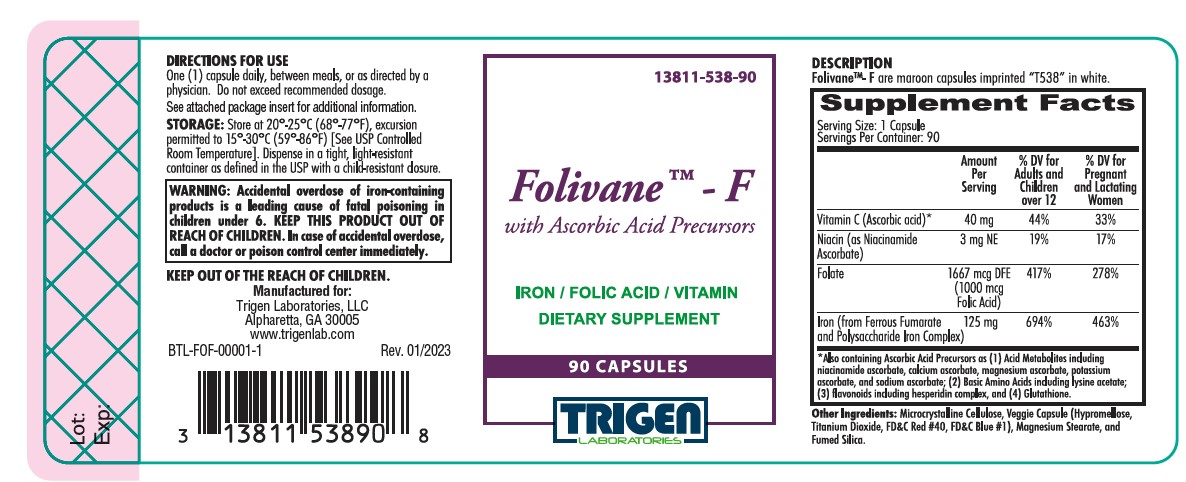 DRUG LABEL: Folivane-F
NDC: 13811-538 | Form: CAPSULE
Manufacturer: Trigen Laboratories, LLC
Category: other | Type: DIETARY SUPPLEMENT
Date: 20230530

ACTIVE INGREDIENTS: FERROUS FUMARATE 62.5 mg/1 1; IRON 62.5 mg/1 1; FOLIC ACID 1 mg/1 1; ASCORBIC ACID 40 mg/1 1; NIACIN 3 mg/1 1
INACTIVE INGREDIENTS: CELLULOSE, MICROCRYSTALLINE; HYPROMELLOSES; MAGNESIUM STEARATE; TITANIUM DIOXIDE; FD&C RED NO. 40; FD&C BLUE NO. 1; SILICON DIOXIDE

Folivane™-F
with Ascorbic Acid Precursors

SUPPLEMENT FACTS

Folivane™-F is a professionally prescribed iron, folic acid, and vitamin supplement used to improve the nutritional status of patients with iron and/or folate deficiency anemia, including women in the prenatal and postnatal period. Do not administer to children under the age of 12.

CONTRAINDICATIONS

Folivane™-F is contraindicated in patients with a known hypersensitivity to any of the ingredients, also, all iron compounds are contraindicated in patients with hemosiderosis, hemochromatosis, or hemolytic anemias. Pernicious anemia is a contraindication, as folic acid may obscure its signs and symptoms.

WARNINGS

WARNING: Accidental overdose of iron-containing products is a leading cause of fatal poisoning in children under 6. KEEP THIS PRODUCT OUT OF REACH OF CHILDREN. In case of accidental overdose, call a doctor or poison control center immediately.

PRECAUTIONS

General: Folic acid alone is improper therapy in the treatment of pernicious anemia and other megaloblastic anemias where B12 is deficient. Anemia requires appropriate investigation to determine its cause or causes. Periodic clinical and laboratory studies are considered essential. Blood tests including hemoglobin and hematocrit should be done to determine the adequacy of therapy. Folic acid should be used with care in the presence of peptic ulcer disease, regional enteritis, and ulcerative colitis. In doses above 0.1 mg daily, folic acid may obscure the diagnosis of pernicious anemia.

USAGE IN PREGNANCY
Before Folivane™-F is prescribed for megaloblastic anemia in pregnancy, appropriate diagnostic exclusion of Addisonian pernicious anemia (due to faulty or blocked absorption of vitamin B12, or extrinsic factor or either a genetic, immunological or surgical basis) should be carried out.

Pediatric Use: Safety and effectiveness of this product have not been established in pediatric patients.

Geriatric Use: Safety and effectiveness of this product have not been established in elderly patients.

ADVERSE REACTIONS

Folic Acid: Allergic sensitizations have been reported following both oral and parenteral administration of folic acid.

Ferrous Fumarate: Gastrointestinal disturbances (anorexia, nausea, diarrhea, constipation, heartburn, and vomiting) occur occasionally, but are usually mild and may subside with continuation of therapy. Reducing the dose and administering it with meals will minimize these effects in the sensitive patient. Iron may turn stools black. This is a harmless effect that is a result of unabsorbed iron. Although the absorption of iron is best when taken between meals, giving Folivane™-F after meals may diminish occasional G.I disturbances. Folivane™-F is best absorbed when taken at bedtime.

OVERDOSAGE

Acute overdosage of iron may cause abdominal pain, nausea and vomiting and, in severe cases, cardiovascular collapse and death. Other more chronic symptoms include pallor and cyanosis, melena, shock, drowsiness, and coma. The estimated overdose of orally ingested iron is 300 mg/kg body weight. Toxic effects are seen at 10-20 mg/kg elemental iron. When overdoses are ingested by children, severe reactions, including fatalities, have resulted. Folivane™-F should be stored beyond the reach of children to prevent against accidental iron poisoning.

DESCRIPTION

Folivane™-F are maroon capsules imprinted "T538" in white.

DIRECTIONS FOR USE

One (1) capsule daily, between meals, or as directed by a physician. Do not exceed recommended dosage.

HOW SUPPLIED

Folivane™-F is supplied in bottle of 90 capsules.
Product Code: 13811-538-90

STORAGE

Store at 20°-25°C (68°-77°F), excursion permitted to 15°-30°C (59°-86°F) [See USP Controlled Room Temperature]. Dispense in a tight, light-resistant container as defined in the USP with a child-resistant closure.

KEEP OUT OF REACH OF CHILDREN.

For use on the order of a healthcare practitioner.

Call your doctor about side effects. To report side effects, call Trigen Laboratories at 1-800-444-5164 or FDA at 1-800-FDA-1088 or www.fda.gov/medwatch.

PLR-FOLF-00001-2 Rev. 05/2023

Manufactured for:

Trigen Laboratories, LLC

Alpharetta, GA 30005

1-770-509-4500

PRINCIPAL DISPLAY PANEL - 90 Capsule Bottle Label

13811-538-90

Folivane™ - F
with Ascorbic Acid Precursors

IRON / FOLIC ACID / VITAMIN
SUPPLEMENT CAPSULES

90 CAPSULES

TRIGEN
LABORATORIES